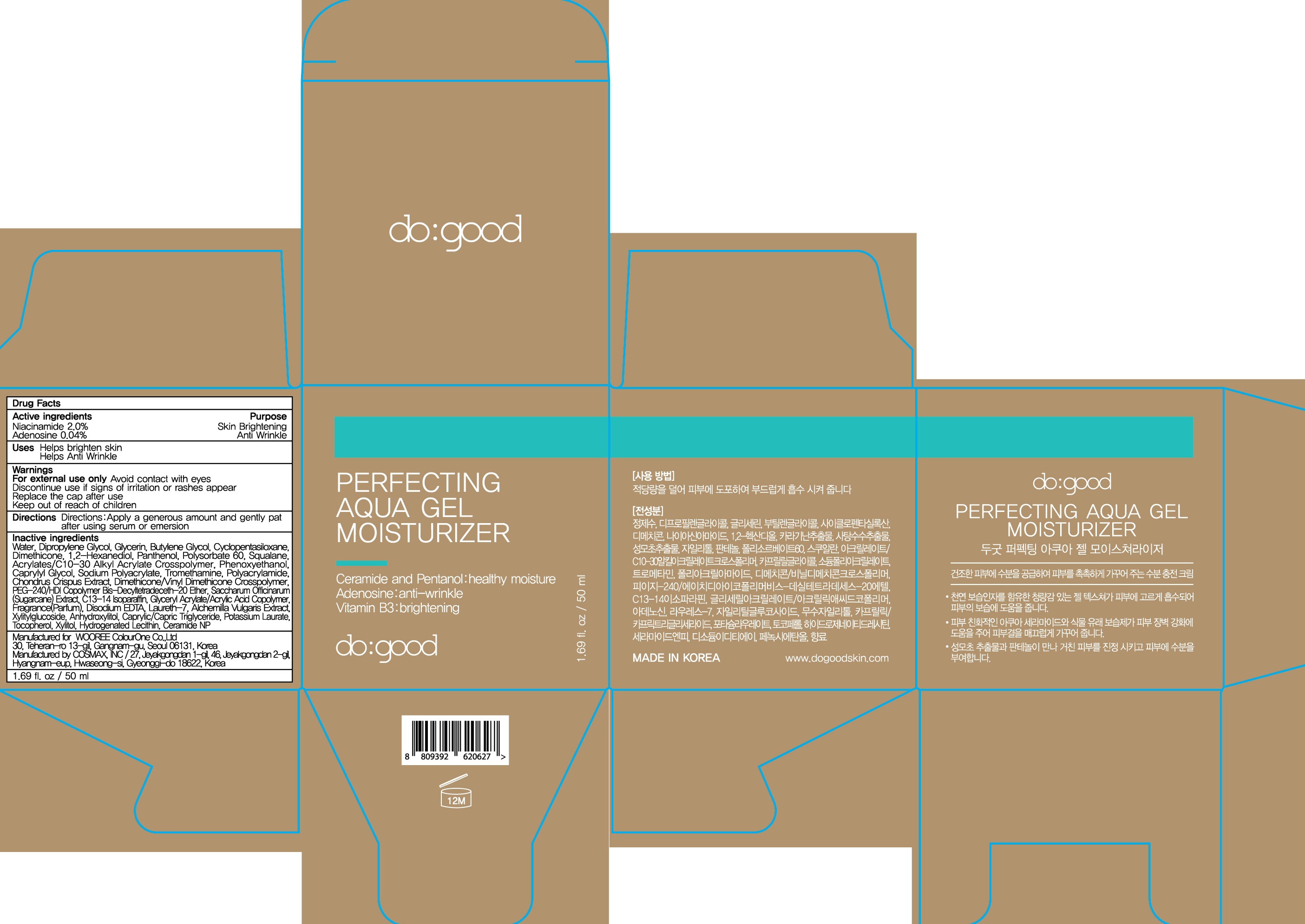 DRUG LABEL: do good Perfecting Aqua Ge l Moisturizer
NDC: 72058-010 | Form: GEL
Manufacturer: WOOREE Colourone Co.,Ltd
Category: otc | Type: HUMAN OTC DRUG LABEL
Date: 20180205

ACTIVE INGREDIENTS: Niacinamide 1.0 g/50 mL; Adenosine 0.02 g/50 mL
INACTIVE INGREDIENTS: Water; Dipropylene Glycol

ACTIVE INGREDIENT

Active Ingredients: Niacinamide 2.0%, Adenosine 0.04%

INACTIVE INGREDIENT

Inactive Ingredients: Water, Dipropylene Glycol, Glycerin, Butylene Glycol, Cyclopentasiloxane, Dimethicone, 1,2-Hexanediol, Panthenol, Polysorbate 60, Squalane, Acrylates/C10-30 Alkyl Acrylate Crosspolymer, Phenoxyethanol, Caprylyl Glycol, Sodium Polyacrylate, Tromethamine, Polyacrylamide, Chondrus Crispus Extract, Dimethicone/Vinyl Dimethicone Crosspolymer, PEG-240/HDI Copolymer Bis-Decyltetradeceth-20 Ether, Saccharum Officinarum (Sugarcane) Extract, C13-14 Isoparaffin, Glyceryl Acrylate/Acrylic Acid Copolymer, Fragrance(Parfum), Disodium EDTA, Laureth-7, Alchemilla Vulgaris Extract, Xylitylglucoside, Anhydroxylitol, Caprylic/Capric Triglyceride, Potassium Laurate, Tocopherol, Xylitol, Hydrogenated Lecithin, Ceramide NP

PURPOSE

Purpose: Skin Brightening, Anti Wrinkle

WARNINGS

Warnings: For external use only. Avoid contact with eyes. Discontinue use if signs of irritation or rashes appear. Replace the cap after use. Keep out of reach of children.

KEEP OUT OF REACH OF CHILDREN

Uses

- Helps brighten skin

- Helps Anti Wrinkle

Directions

Directions: Apply a generous amount and gently pat after using serum or emersion.